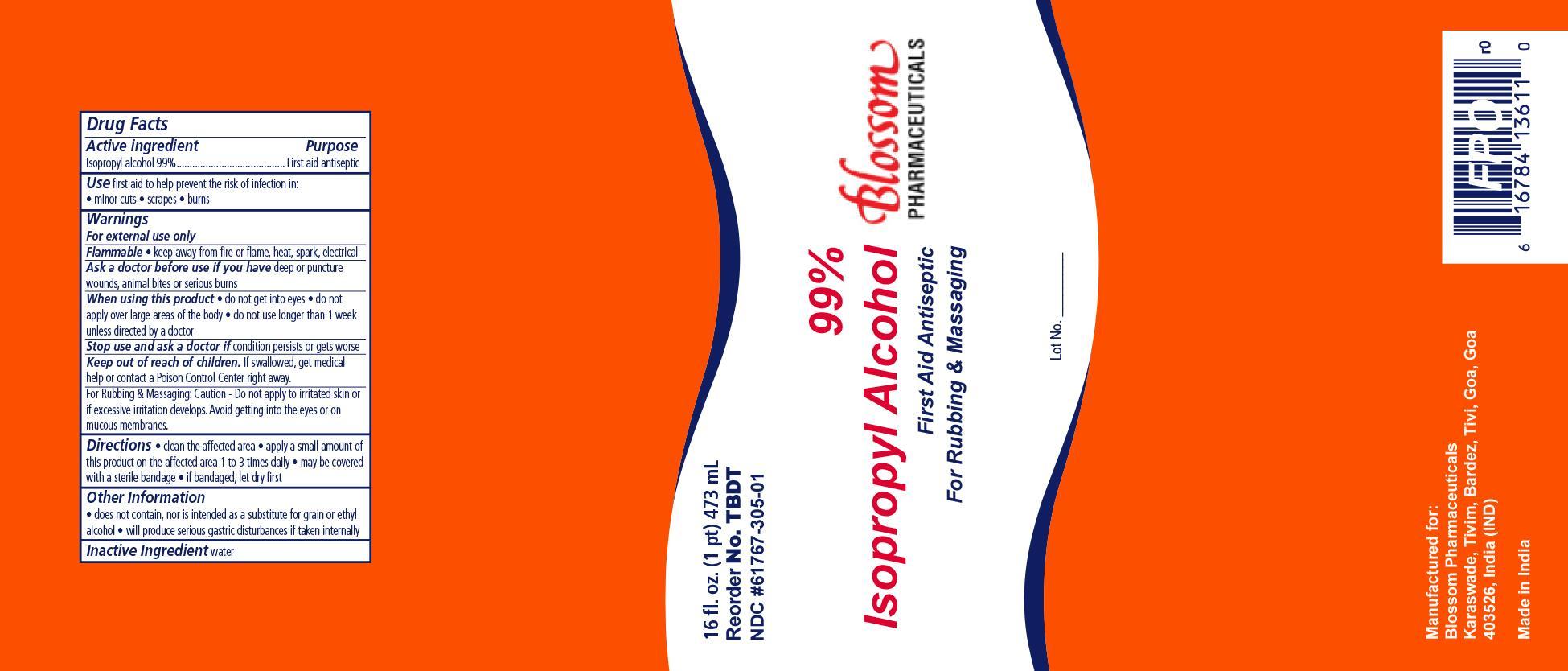 DRUG LABEL: Alcohol
NDC: 61767-305 | Form: LIQUID
Manufacturer: Blossom Pharmaceuticals
Category: otc | Type: HUMAN OTC DRUG LABEL
Date: 20140131

ACTIVE INGREDIENTS: ISOPROPYL ALCOHOL 0.99 mL/1 mL
INACTIVE INGREDIENTS: WATER

Alcohol 99%

Active Ingredient Purpose

Isopropyl Alcohol 99% v/v Antiseptic

PURPOSE

First aid to help prevent the risk of infection in:

- minor cuts
- scrapes
- burns

WARNINGS

- For external use only
- Flammable, keep away from fire or flame, heat, spark, electrical.
- Not for use with electrocautinary devices or procedures
- Ask a doctor before use if you have deep puncture wounds, animal bites or serious burns.
- Stop use and ask a doctor if condition persist or gets worse.

For rubbing and massaging:

- Caution: Do not apply to irritated skinor if excessive irritation develops
- Avoid getting into eyes or mucous membranes

INDICATIONS & USAGE

When using this product:

- do not get in eyes
- do not apply over large areas of the body
- do not use longer than 1 week unless directed by a doctor

KEEP OUT OF REACH OF CHILDREN

IIf swallowed, get medical help or contact a Poison Control Center right away.

DOSAGE & ADMINISTRATION

DIRECTIONS:

- clean the affected area
- apply a small amount of this product on the affected area 1 to 3 times daily
- may be covered with a sterile bandage
- if bandaged let dry first

OTHER INFORMATION

- Store at room temperature: 15 deg C to 30 deg C 59 deg F to 86 deg F
- avoid excessive heat
- Does not contain, nor is it intended as a substitute for grain or ethyl alcohol
- Will produce serious gastric disturbances if taken internally

INACTIVE INGREDIENT

- Water

PRINCIPAL DISPLAY PANEL

DYNAREX 99% ISOPROPYL ALCOHOL

99 IPA BP.jpg